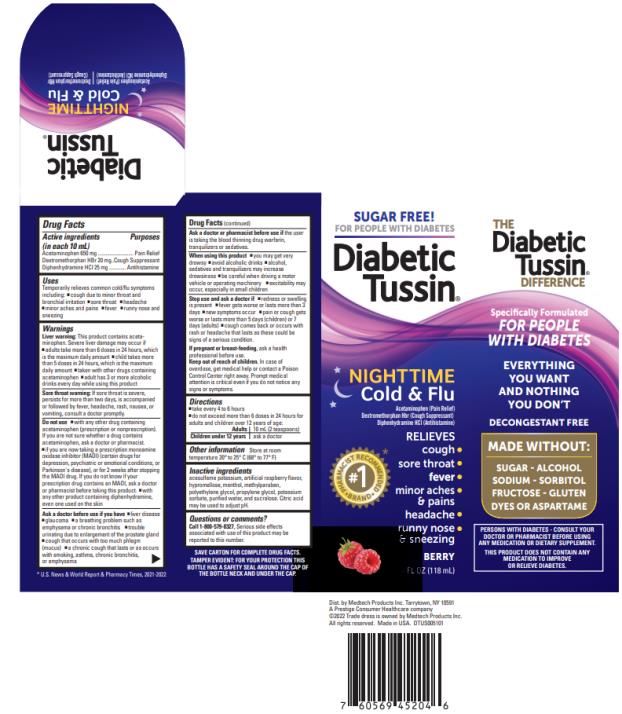 DRUG LABEL: Diabetic Tussin Nighttime Cold and Flu
NDC: 61787-516 | Form: LIQUID
Manufacturer: MEDTECH PRODUCTS INC
Category: otc | Type: HUMAN OTC DRUG LABEL
Date: 20220303

ACTIVE INGREDIENTS: ACETAMINOPHEN 650 mg/10 mL; DEXTROMETHORPHAN HYDROBROMIDE 20 mg/10 mL; DIPHENHYDRAMINE HYDROCHLORIDE 25 mg/10 mL
INACTIVE INGREDIENTS: ACESULFAME POTASSIUM; HYPROMELLOSE, UNSPECIFIED; MENTHOL, UNSPECIFIED FORM; METHYLPARABEN; POLYETHYLENE GLYCOL 400; POTASSIUM SORBATE; PROPYLENE GLYCOL; RASPBERRY; WATER; ANHYDROUS CITRIC ACID

Diabetic Tussin Nighttime Cold and Flu 61787-516

Drug Facts

Active ingredients (in each 10 mL)

Acetaminophen 650 mg

Dextromethorphan HBr 20 mg

Diphenhydramine HCl 25 mg

Purposes

Pain Relief

Cough Suppressant

Antihistamine

Uses

temporarily relieves common cold/flu symptoms including:

- cough due to minor throat and bronchial irritation
- sore throat
- headache
- minor aches and pains
- muscular aches
- fever
- runny nose and sneezing

Warnings

Liver warning: This product contains acetaminophen. Severe liver damage may occur if

- adults take more than 6 doses in 24 hours, which is the maximum daily amount
- child takes more than 5 doses in 24 hours, which is the maximum daily amount
- taken with other drugs containing acetaminophen
- adult has 3 or more alcoholic drinks everyday while using this product

Sore throat warning: If sore throat is severe, persists for more than two days, is accompanied or followed by fever, headache, rash, nausea, or vomiting, consult a doctor promptly.

Ask a doctor before use if you have

- liver disease
- glaucoma
- a breathing problem such as emphysema or chronic bronchitis
- trouble urinating due to enlargement of the prostate gland
- cough that occurs with too much phlegm (mucus)
- a chronic cough that lasts or as occurs with smoking, asthma, chronic bronchitis, or emphysema

Ask a doctor or pharmacist before use

if the user is taking the blood thinning drug warfarin, tranquilizers or sedatives.

When using this product:

- you may get very drowsy
- avoid alcoholic drinks
- alcohol, sedatives and tranquilizers may increase drowsiness
- be careful when driving a motor vehicle or operating machinery
- excitability may occur, especially in small children

Stop use and ask a doctor if

- redness or swelling is present
- fever gets worse or lasts more than 3 days
- new symptoms occur
- pain or cough gets worse or lasts more than 5 days (children) or 7 days (adults)
- cough comes back or occurs with rash or headache that lasts

These could be signs of a serious condition.

If pregnant or breast-feeding,

ask a health professional before use.

Keep out of reach of children.

In case of overdose, get medical help or contact a Poison Control Center right away. Prompt medical attention is critical even if you do not notice any signs or symptoms.

Directions

- take every 4 to 6 hours
- do not exceed more than 6 doses in 24 hours for adults and children over 12 years of age

Adults | 10 mL (2 teaspoons)
Children under 12 years | ask a doctor

Other information

- Store at room temperature 20-25°C (68-77°F)

Inactive ingredients

Acesulfame potassium, artificial raspberry flavor, hypromellose, menthol, methylparaben, polyethylene glycol, potassium sorbate, propylene glycol, purified water, and sucralose. Citric acid may be used to adjust pH.

Questions or comments?

Call: 1-800-579-8327, serious side effects associated with use of this product may be reported to this number.

Package/Label Principal Display Panel

SUGAR & ALCOHOL FREE!

Specifically Formulated for Diabetics

Diabetic Tussin®

NIGHTTIME

COLD & FLU

Acetaminophen (Pain Relief)

Dextromethorphan HBr (Cough Suppressant)

Diphenhydramine HCl (Antihistamine)

Relieves:

- Cough
- Sore throat
- Runny nose & sneezing
- Minor aches & pains
- Headache
- Fever

Improved Berry Flavor

4 FL OZ (118 mL)